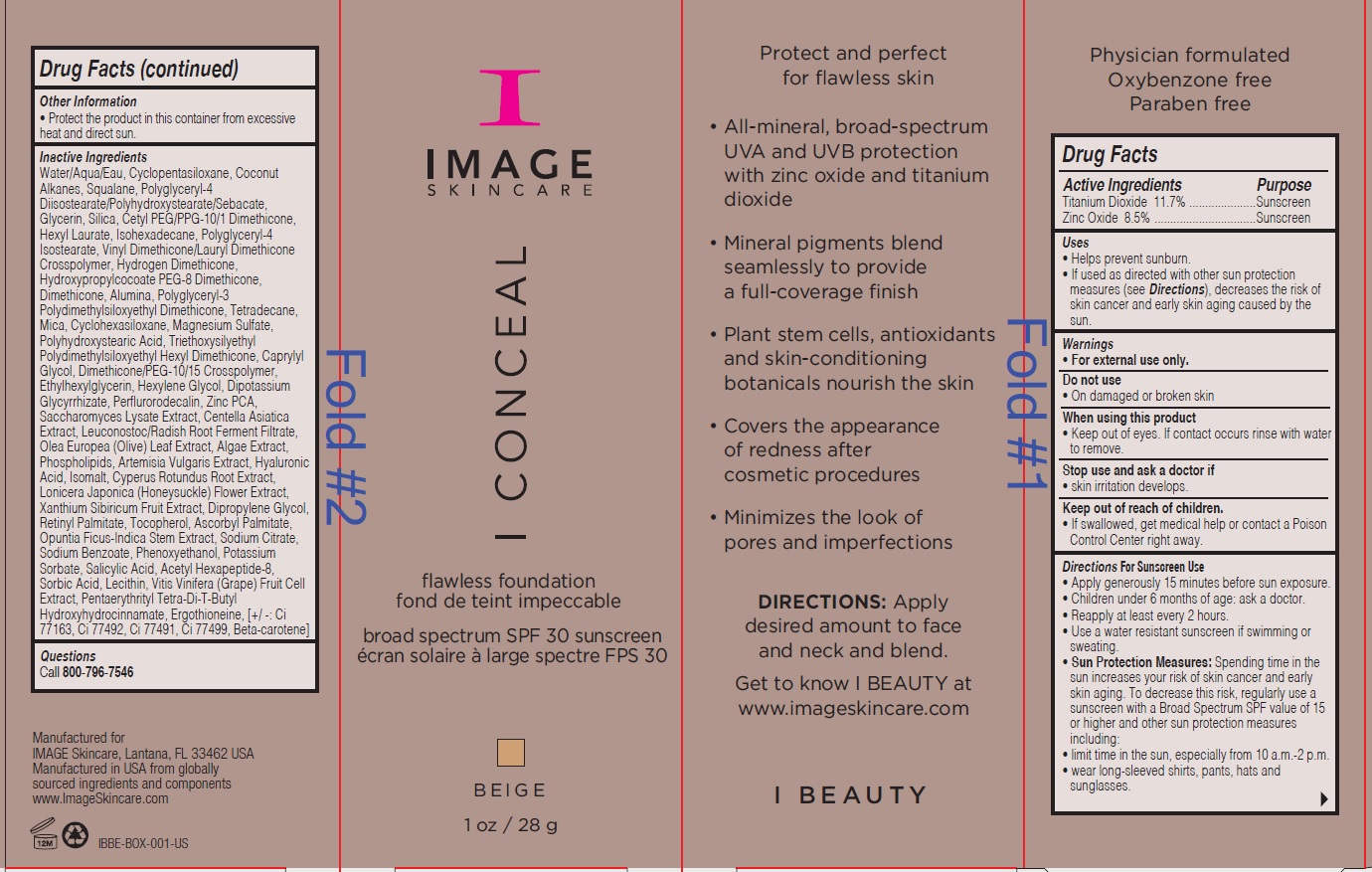 DRUG LABEL: I Conceal Flawless Foundation Broad Spectrum SPF 30 Sunscreen Beige
NDC: 62742-4172 | Form: CREAM
Manufacturer: Allure Labs Inc
Category: otc | Type: HUMAN OTC DRUG LABEL
Date: 20191004

ACTIVE INGREDIENTS: ZINC OXIDE 85 mg/1 g; TITANIUM DIOXIDE 117 mg/1 g
INACTIVE INGREDIENTS: WATER; CYCLOMETHICONE 5; COCONUT ALKANES; SQUALANE; GLYCERIN; SILICON DIOXIDE; CETYL PEG/PPG-10/1 DIMETHICONE (HLB 2); HEXYL LAURATE; ISOHEXADECANE; POLYGLYCERYL-4 ISOSTEARATE; DIMETHICONE/VINYL DIMETHICONE CROSSPOLYMER (SOFT PARTICLE); HYDROGEN DIMETHICONE (13 CST); DIMETHICONE; ALUMINUM OXIDE; POLYGLYCERYL-3 POLYDIMETHYLSILOXYETHYL DIMETHICONE (4000 MPA.S); TETRADECANE; MICA; CYCLOMETHICONE 6; MAGNESIUM SULFATE, UNSPECIFIED FORM; POLYHYDROXYSTEARIC ACID (2300 MW); CAPRYLYL GLYCOL; ETHYLHEXYLGLYCERIN; HEXYLENE GLYCOL; GLYCYRRHIZINATE DIPOTASSIUM; PERFLUNAFENE; ZINC PIDOLATE; SACCHAROMYCES LYSATE; CENTELLA ASIATICA; LEUCONOSTOC/RADISH ROOT FERMENT FILTRATE; OLEA EUROPAEA LEAF; LAMINARIA DIGITATA; LECITHIN, SOYBEAN; ARTEMISIA VULGARIS WHOLE; HYALURONIC ACID; ISOMALT; CYPERUS ROTUNDUS TUBER; LONICERA JAPONICA FLOWER; XANTHIUM SIBIRICUM FRUIT; DIPROPYLENE GLYCOL; VITAMIN A PALMITATE; TOCOPHEROL; ASCORBYL PALMITATE; OPUNTIA FICUS-INDICA STEM; SODIUM CITRATE; SODIUM BENZOATE; PHENOXYETHANOL; POTASSIUM SORBATE; SALICYLIC ACID; ACETYL HEXAPEPTIDE-8; SORBIC ACID; WINE GRAPE; PENTAERYTHRITOL TETRAKIS(3-(3,5-DI-TERT-BUTYL-4-HYDROXYPHENYL)PROPIONATE); ERGOTHIONEINE; BISMUTH OXYCHLORIDE; FERRIC OXIDE YELLOW; FERROSOFERRIC OXIDE; BETA CAROTENE

DRUG FACTS

Active Ingredients:

Zinc Oxide - 8.5%

Titanium Dioxide - 11.7%

Purpose: Sunscreen

Uses:

- Helps prevent sunburn.
- If used as directed with other sun protection measures (see Direction), decreases the risk of skin cancer and early skin aging caused by the sun.

Warning:

- For external use only.

Do not use:

- on damaged or broken skin.

When using this products:

- Keep out of eyes. If contact occurs rinse with water to remove.

Stop use and ask a doctor

- if skin irritation develops.

Keep out of reach of children:

- If swallowed, get medical help or contact a Poison Control Center right away.

DOSAGE AND ADMINISTRATION

Directions for Sunscreen use:

- Apply generously 15 minutes before sun exposer.
- Children under 6 months of age: ask a doctor.
- Reapply at least every 2 hours.
- Use a water resistant sunscreen if swimming or sweating.
- Sun protection measures.Spending time in the sun increase your risk of skin cancer and early skin aging. To decrease the risk, regularly use a sunscreen with a Broad Spectrum SPF value of 15 or higher and other sun protection measures including:
- limit time in the sun, especially from 10 a.m. - 2 p.m.
- wear long sleeve shirts, pants, hats and sunglasses.

INACTIVE INGREDIENT

Inactive Ingredients: Water/Aqua/Eau, Cyclopentasiloxane, Coconut Alkanes, Squalne, Polyglyceryl-4 Diisostearate/Polyhydroxystearate/ Sebacate, Glycerin, Silica, Cetyl PEG/PPG-10/1 Dimethicone, Hexyl Laurate, Isohexadecane, Polyglyceryl-4 Isostearate, Vinyl Dimethicone/Lauryl Dimethicone, Dimethicone, Hydroxypropylcocoate PEG-8 Dimethicone, Alumina, Polyglyceryl-3 Polydimethylsiloxyethyl Dimethicone, Tetradecane, Mica, Cyclohexasiloxane, Magnesium Sulfate, Polyhydroxystearic Acid, Triethoxysilyethyl Polydimethylsiloxyethyl Hexyl Dimethicone, Caprylyl Glycol, Dimethicone/PEG-10/15 Crosspolymer, Ethylhexylglycerin, Hexylene Glycol, Dipotassium Glycyrrhizate, Perflurorodecalin, Zinc PCA, Saccharomyces Lysate Extract, Centella Asiatica Extract, Leuconostoc/Radish Root Ferment Filtrate, Olea Europa (Olive) Leaf Extract, Algae Extract, Phospholipids, Artemisia Vulgaris Extract, Hyaluronic Acid, Isomalt, Cyperus Rotundus Root Extract, Lonicera Japonica (Honeysuckle) Flower Extract, Xanthium Sibiricum Fruit Extract, Dipropylene Glycol, Retinyl Palmitate, Tocopherol, Ascorbyl Palmitate, Opuntia Ficus-Indica Stem Extract, Sodium Citrate, Sodium Benzoate, Phenoxyethanol, Potassium Sorbate, Salicylic Acid, Acetyl Hexapeptide-8, Sorbic Acid, Lecithin, Vitis Vinifera (Grape) Fruit Cell Extract, Pantearythrityl Tetra-Di-T-Butyl Hydroxyhydrocinnamate, Ergothionine, [+/-: Ci 77163, Ci 77492, Ci 77491, Ci 77499, Beta-carotene].

PACKAGE LABEL

Manufactured for:

IMAGE Skincare, Lantana, FL 33462 USA

Manufactured in USA from globally

sourced ingredients and components

www.ImageSkincare.com